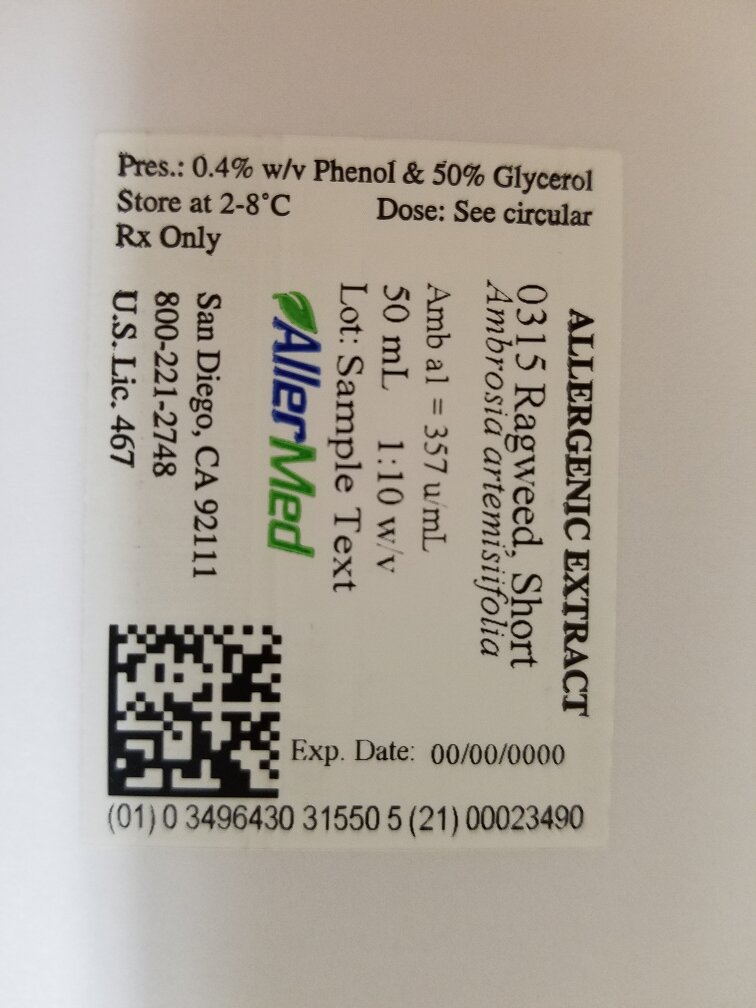 DRUG LABEL: Short Ragweed
NDC: 49643-315 | Form: INJECTION
Manufacturer: Allermed Laboratories, Inc.
Category: prescription | Type: HUMAN PRESCRIPTION DRUG LABEL
Date: 20250117

ACTIVE INGREDIENTS: AMBROSIA ARTEMISIIFOLIA POLLEN 1 g/10 mL
INACTIVE INGREDIENTS: GLYCERIN 5.3 mL/10 mL; PHENOL 0.4 g/10 mL; WATER; SODIUM CHLORIDE 0.25 g/10 mL; SODIUM BICARBONATE 0.125 g/10 mL

ALLERGENIC EXTRACT Standardized Short Ragweed

DESCRIPTION

INGREDIENTS - Allergenic extract of short ragweed pollen is a clear, amber-colored solution prepared from the dry, defatted pollen of Ambrosia elatior. The extract contains the water extractables of the pollen, 0.25% sodium chloride, 0.125% sodium bicarbonate, 0.5% phenol and 50% glycerol by volume. Extract of mixed short-giant ragweed has the same appearance as short ragweed pollen extract and contains the same chemical ingredients. It is prepared from equal gram weights of the pollens of Ambrosia elatior and Ambrosia trifida.
STANDARDIZATION - The potency of ragweed pollen extract is based on antigen E, a protein component which is believed to be the most important allergen of short ragweed pollen. Extracts of short ragweed pollen sold in the U.S. must have a minimum antigen E content of 67.5 units per ml for a 1:20 w/v concentrate. Extracts of mixed short-giant ragweed must have a minimum antigen E content of 33.75 units/ml for a 1:20 w/v concentrate. The importance of antigen E in ragweed allergy is based on the following observations:

1. In vitro studies with antigen E have shown that it is capable of causing histamine release from peripheral leukocytes of ragweed sensitive persons^1.
2. The antigen E content of short ragweed pollen extract has been found to correlate with extract potency when measured by skin test response in persons allergic to short ragweed pollen^2.
3. Immunotherapy with antigen E has been shown to be comparably effective to whole short ragweed pollen extract in reducing symptoms related to ragweed pollen exposure^3.

The weight by volume value shown on the label is a measurement of extract concentration, rather than extract potency. Weight by volume designations may be used to identify dilutions of extract for skin testing and immunotherapy, and are useful from a practical standpoint in identifying the relative strength of a given extract. However, studies have shown that the antigen E content varies in extracts with the same weight by volume concentration^4.
EXPIRATION DATING - Expiration dating is based on the antigen E content of the extract. Extracts containing 50% glycerol by volume have longer dating periods due to the protective effects of glycerol on antigen E^(5, 6). The expiration period of aqueous concentrate and saline dilutions of glycerinated concentrate is approximately one-half that of glycerinated extract containing comparable antigen E content.
Ragweed extract should be kept at 2°C to 8°C during use and office storage to retain potency. Higher temperatures have an adverse affect on antigen E.

INDICATIONS

Studies have shown that properly performed an interpreted skin tests with ragweed pollen extract are useful in the diagnosis of allergy to ragweed pollen^(7, 8, 20, 21). Immunotherapy with the appropriate dosage of short ragweed pollen extract is effective in reducing symptoms of hay fever and asthma resulting from exposure to short ragweed pollen (9, 10, 11), and it is believed to be effective with extract of giant ragweed, although carefully controlled studies are unavailable. However, clinical observations and known cross reactivity between short and giant ragweed pollens have led to the practice of using a mixture of the two species for skin testing and treatment^(22, 23, 24, 25, 26, 27).
This form of treatment is recommended for patients who cannot avoid exposure to pollen and who do not obtain satisfactory relief of symptoms from other medications, such as antihistamines. Immunologic changes resulting from treatment with short ragweed pollen extract are believed to include:

1. The induction of specific anti-ragweed IgG antibodies commonly referred to as "blocking antibodies"^(12, 13).
2. A decrease in the elevation of ragweed specific IgE during and immediately following the ragweed pollen season^14.
3. A reduction of circulating anti-ragweed IgE after long-term immunotherapy^15.
4. A decrease in skin reactivity to the extract^16 and a decrease in leukocyte sensitivity to histamine release^17 after long-term immunotherapy.

CONTRAINDICATIONS

There are no absolute contraindications to the use of ragweed pollen extract in the diagnosis and treatment of ragweed allergy. When used in accordance with accepted principles of skin testing and immunotherapy, the extract is considered safe and effective. Relative contraindications include (1) extreme sensitivity to the extract as demonstrated by previous anaphylaxis following skin testing or subcutaneous injection, (2) recent myocardial infarction, and (3) pregnancy (see Precautions #4). The benefit to risk ration must be evaluated in each of the above situations. Ragweed pollen extract should not be administered to persons who are not sensitive to ragweed pollen

WARNINGS

Physicians who elect to administer ragweed pollen extract should be familiar with the clinical use of allergenic extracts and have the necessary emergency equipment and medication available to treat systemic allergic reactions.
The injection of ragweed pollen extract may cause severe local and/ or systemic anaphylactic reactions in some individuals. To minimize this potential hazard, the relative sensitivity of the patient must be assessed from the allergic history and from clinical observations. Patients should be informed of this risk prior to skin testing and immunotherapy (see adverse reactions).
The dosage must be reduced when starting a patient on fresh standardized (Antigen E) extract or when transferring a patient from non-standardized to standardized extract, even though the labeled strength of the old and new vials may be the same. This is necessary due to a loss of extract potency during storage in the physician's office. The antigen E content of old and new extract must be compared and adjusted by dosage reduction and/or dilution before new extract is administered. The amount of new extract given from the old vial, assuming both extracts contain comparable amounts of antigen E. Any evidence of a local or generalized reaction requires a reduction in dosage during the initial stages of hyposensitization as well as during maintenance therapy.

PRECAUTIONS

1. Extract must be stored at 2°C to 8°C to retain potency. Storage at this temperature should be observed as closely as possible, since higher temperatures adversely affect the antigen E content of the product. Extract should not be left at room temperature for the purpose of making dilutions or mixing with other allergenic materials, unless precautions are taken to maintain the recommended temperature using special cooling trays or other suitable methods.
2. Extract should be administered with autoclaved or sterile disposable syringes, needles and testing devices to prevent the transmission of homologous serum hepatitis and other infectious agents from person to person.
3. Extract may cause local or generalized reactions. Physicians who administer the product should be familiar with the principles and practice of allergy and should have epinephrine HCL 1:1,000, as well as other emergency medication and equipment available to treat anaphylaxis. Persons receiving extract by skin test or by subcutaneous injection for treatment must be instructed to remain in the physician's office for 20 minutes following testing or immunotherapy, and to return immediately to the office if any signs of a generalized allergic reaction occur, including hives, symptoms of hay fever, and/ or asthma.
4. PREGNANCY CATEGORY C. ragweed pollen extract. Animal reproduction studies have not been conducted with ragweed pollen extract. It is also not known whether ragweed pollen extract can cause fetal harm when administered to a pregnant woman or can affect reproduction capacity. Ragweed pollen extract should be given to a pregnant woman only if clearly needed.

ADVERSE REACTIONS

LOCAL REACTIONS. The occurrence of a hive 5 to 15 minutes after injection is usually due to leakage of extract into the skin along the needle tract. Firm pressure (not rubbing) at the site of injection immediately after withdrawal of the needle will usually prevent this reaction. It does not require a reduction in dosage. A strong local reaction with erythema and edema which persists at the injection site for several hours indicates that too much extract has been given. Failure to note this response may result in a serious generalized reaction. Treatment should be altered as follows:

1. Additional injections should not be given until all evidence of the reaction has disappeared.
2. The dosage should be reduced three levels, e.g., from 0.4 cc to 0.5 cc or the equivalent, and held at that level for two or three treatments.

A second reaction at or near the dose which caused the first local response indicates that a maximum tolerated amount of extract has been reached and no further increases in dosage should be attempted. Maintenance therapy should be continued thereafter at the highest possible non-reacting dose.
SYSTEMIC REACTIONS. Systemic (generalized) reactions may range from a mild exaggeration of the patient's allergic symptoms to hives, anaphylactic shock, or even death from anaphylaxis. Systemic reactions may occur when a previous local reaction has not been heeded, or when the extract is accidentally injected intravenously. The reaction usually occurs 5 to 20 minutes after injection. Symptoms may include sneezing, coughing, itching, shortness of breath, abdominal cramps, vomiting, diarrhea, tachycardia, hypotension, and respiratory failure in severe cases. The reaction is usually stopped by the subcutaneous injection of epinephrine HCL 1:1,000 (See Overdosage below). The oral administration of antihistamines and the placement of a tourniquet proximal to the injection site are helpful adjuncts. In the event that additional measures are required, it may be necessary to treat the patient for bronchospasm with intravenous aminophylline, intravenous fluids and corticosteroids; for hypotension with vasopressors, volume repletion, isoproterenol and corticosteroids; for laryngeal obstruction with oxygen and tracheostomy and for cardiac arrest with cardiopulmonary resuscitation and other appropriate measures.

DOSAGE AND ADMINISTRATION

DIAGNOSIS. If the extract supplied in this package is concentrated product (w/v 1:20), it should not be used for intradermal testing. Concentrated extract may be used for scratch or prick testing providing the patient is not exposed to high levels of ragweed pollen and experiencing pronounced symptoms of hay fever or asthma at the time of testing. Extract for intradermal testing must be diluted to a strength of 0.25 units of antigen E per ml^7. Skin tests should not be performed if the patient has taken antihistamine within 24 hours prior to testing.
PROCEDURES
Scratch Test: 1 drop of extract concentrate applied to a small scratch or scarification of the volar surface of the forearm or the flat aspect of the back.
Prick Test: 1 drop of extract concentrate applied to the unbroken skin of the forearm or the back followed by pricking the skin under the drop.
Intradermal Test: 0.05 ml of extract containing 0.25 antigen E units per ml given intradermally on the volar surface of the forearm or outer aspect of the upper arm. This test should not be performed unless the patient is negative to a properly administered and interpreted scratch or prick test. A final intradermal test using 0.05 ml of extract containing 2.5 antigen E units per ml may be used to rule out skin sensitivity to ragweed allergen.
INTERPRETATION OF RESULTS
Scratch and Prick Test
A negative test shows only a slight red area at the site of scarification or prick penetration. Positive tests are scored as follows:
1+ Erythema with 5 mm wheal
2+ Erythema with 5 - 10 mm wheal
3+ Erythema with a 10 - 15 mm wheal
4+ Erythema with a wheal 15 mm (or larger) with pseudopodia
Intradermal Test
A negative test shows no change in the appearance and size of the 5 mm wheal created by the I.D. injection of 0.05 ml of extract. Positive tests are scored as follows:
1+ Erythema with 10-20 mm with a 5-10 mm wheal
2+ Erythema with 20-30 mm with a 5-10 mm wheal
3+ Erythema with 30-40 mm with a 10-15 mm wheal
4+ Erythema greater than 40 mm with a 15 mm wheal (or larger) with pseudopodia
IMMUNOTHERAPY
Concentrated ragweed extract must be diluted before administration to new patients. As a rule, extract containing 0.01 to 0.05 units of antigen E per ml are safe to initiate immunotherapy. An intradermal skin test with the intended starting dose may be done as an additional precaution in evaluating the patient's sensitivity.
Injections should be given subcutaneously in the outer aspect of the upper arm. Care must be taken to avoid injecting the extract into a blood vessel, because of the potential hazard of anaphylaxis. Concentrated extract is usually administered once every two to four weeks at a maximum dose of 0.2 ml. A mild burning sensation immediately following the injection of concentrated extract is due to the glycerol in the extract. It should not be interpreted as an adverse allergic response. A suggested dosage schedule is shown in the Table below.
Patients who have received allergenic extract for maintenance therapy should not be given the same dose from a fresh vial of extract. The antigen E content of ragweed pollen extract varies from lot to lot. Although the potency of fresh extract can be compared with that of previously administered product and adjusted accordingly, it is advisable to reduce the dosage of fresh extract to one-half the amount give from a previous lot. The antigen E content of ragweed pollen extract diminishes during storage and use in the physician's office, and, therefore, may be less than that specified on the vial label. In addition, ragweed pollen extract contains other components which may contribute to the overall allergenicity of the product^18.
SUGGESTED DOSAGE SCHEDULE FOR RAGWEED EXTRACT BASED ON ANTIGEN E CONCENTRATION (units per ml)
Concentrated extracts (w/v 1:20) of short ragweed pollen usually contain between 100 and 300 units antigen E per ml. Mixed short-giant ragweed pollen extracts contain approximately one-half these values.

AgE Units 0.01/ml frequency twice weekly | AgE Units 0.1/ml frequency twice weekly | AgE Units 1.0/ml frequency twice weekly | AgE Units 10/ml frequency twice weekly | AgE Units 100/ml frequency twice weekly
No. ml | No. ml | No. ml | No. ml | No. ml
1 0.025 | 1 0.025 | 1 0.025 | 1 0.025 | 1 0.025
2 0.05 | 2 0.05 | 2 0.05 | 2 0.05 | 2 0.05
3 0.10 | 3 0.10 | 3 0.10 | 3 0.10 | 3 0.10
4 0.15 | 4 0.15 | 4 0.15 | 4 0.15 | 4 0.15
5 0.20 | 5 0.20 | 5 0.20 | 5 0.20 | 5 0.20
6 0.25 | 6 0.25 | 6 0.25 | 6 0.25 | 6 0.25
7 0.30 | 7 0.30 | 7 0.30 | 7 0.30 | 7 0.30

Note: Do not exceed a dose of 0.2 ml if the extract being administered contains 50% glycerol by volume
Studies^(10, 11) have shown that the accumulated pre-seasonal dose of short ragweed pollen extract should be in the range of 250 to 1000 units of antigen E to effectively reduce ragweed-related symptoms^(3, 19). This dosage of antigen E is contained in 2.5 ml to 10.0 ml of extract containing 100 antigen E units/ml. Treatment with a maximum tolerated dose is recommended for both short ragweed pollen extract and mixed short-giant ragweed extract.
The maintenance dose of ragweed pollen extract is defined as the highest tolerated dose that is consistently well tolerated without undue pain or swelling and which provides maximum relief to symptoms. The interval between maintenance injections should not exceed 4 weeks, since tolerance to the extract may be lost at longer intervals. If the interval exceeds 4 weeks, the dosage should be reduced by one-half for every additional two week period. A reduction in the maintenance dose also may be necessary during the ragweed season, due to the overdosing effects of inhaled allergen combined with injected allergen. As a rule, it is advisable to reduce the dosage by one-half during ragweed pollination and to increase the frequency of injections as needed to provide adequate relief symptoms. The dosage of ragweed pollen extract given to children is the same as the adult dose except for slight modifications due to body size and weight. A child's dose of 0.2 ml is considered comparable to an adult dose of 0.5 ml of the same dilution. Maintenance injection should be continued for a period of two to three years or longer, depending upon patient tolerance and clinical response.

OVERDOSAGE

A local reaction characterized by erythema and edema that persists for several hours or longer, or a recurrence of allergic symptoms following an injection requires that the dosage be reduced. Additional extract should not be given until all evidence of a previous reaction has disappeared.
Severe generalized symptoms or anaphylaxis following an injection must be treated immediately with epinephrine HCL 1:1000 as follows: Usual Dosage - Children under 12 years 0.1 to 0.2 cc; persons over 12 years 0.3 to 0.5 cc, repeated as necessary every 10 to 15 minutes. Intravenous antihistamines and hydro-cortisone also may be used, but only after sufficient epinephrine has been give. (see Adverse Reaction Systemic).
Immunotherapy after anaphylaxis should only be considered if the probable cause of anaphylaxis can be identified, such as accidental intravenous injection or failure to reduce the dosage after a previous local reaction or during periods of high external exposure to ragweed pollen.

SUPPLIED

Short ragweed pollen extract and mixed short-giant ragweed pollen extract in concentrated form (w/v 1:20) are supplied in 1 ml dropper vials for scratch or prick testing and in 10 ml, and 50 ml vials for bulk use. Dilutions other than 1:20 w/v may be custom ordered.

REFERENCES

1. Norman, P.S. and L.M. Lichtenstein. Capacity of purified antigens and whole pollen extracts to release histamine from leukocytes of hay fever patients. J. Allergy and Clinical Immunology. 52:94, 1973.
2. Gleich, G.J., J.B. Larson, R.T. Jones and H. Baer. Measurement of the potency of allergenic extracts by their inhibitory capacities in the radioallergosorbent test. J. Allergy and Clinical Immunology. 53:158, 1974.
3. Norma, P.S., W.L. Winkenwerder and L. Lichtenstein. Immunotherapy of hay fever with ragweed antigen E: comparisons with whole pollen extract and placebos. J. Allergy. 42:93, 1968.
4. Baer, H., H. Godfrey, C.J. Maloney, P.S. Norman, and L.M. Lichtenstein. The potency and antigen E content of commercially prepared ragweed extracts. J. Allergy. 45:347, 1970.
5. Center, J.G., N. Shuller and L.D. Zeleznick. Stability of antigen E in commercially prepared ragweed pollen extracts. J. Allergy and Clinical Immunology. 54:305, 1974.
6. Hiatt, C.W., H. Baer, and M.L. Hooton. Kinetics of thermal decay of antigen E from short ragweed pollen. J. Biological Standardization. 5:39, 1977.
7. Norman, P.S., L.M. Lichtenstein and K. Ishizaka. Diagnostic tests in ragweed hay fever. J. Allergy and Clinical Immunology. 52:210, 1973.
8. Bruce, C.A., R.R. Rosenthal, L.M. Lichtenstein and P.S. Norman. Diagnostic tests in ragweed-allergic asthma. J. Allergy and Clinical Immunology. 53:230, 1974.
9. Lowell, F.C. and W. Franklin. A double-blind study of the effectiveness and specificity of injection therapy in ragweed hay fever. New England Journal of Medicine. 273:675, 1965.
10. Franklin, W. and F.C. Lowell. Comparison of two dosages of ragweed extract in the treatment of pollinosis. J.American Medical Association. 201:915, 1967.
11. Johnstone, D.E. Study of the role of antigen dosage in the treatment of pollinosis and pollen asthma. American Medical Association, Journal of Diseases of Children. 94:1, 1957.
12. Levy, D.A., L.M. Lichtenstein, E.O. Goldstein and K. Ishizaka. Immunologic and cellular changes accompanying the therapy of pollen allergy. J. Clinical Investigations. 50:360, 1971.
13. Melam, H.L., J.J. Purzansky, R. Patterson and S. Singer. Clinical and immunologic studies of ragweed immunotherapy. J. Allergy. 47:262, 1971.
14. Levy, D.A. and A.G. Osher. Studies on the mechanism of hypersensitivity phenomena. XVI. In vitro assays of reaginic activity in human sera: effect of therapeutic immunization on seasonal titer changes. J. of Immunology. 99:1068, 1967.
15. Connell, J.T. and W.B. Serman. Changes in skin - sensitizing antibody titer after injections of aqueous pollen extract. J. of Allergy. 43:22, 1969.
16. Sprecace, G.A., S.G. Pomper, W.B. Sherman, A. Lemlich and H. Ziffer. The effects of antigen injections on skin reactivity to antigens. J. Allergy. 38:9, 1966.
17. Pruzansky, J.J. and R. Patterson. Histamine release from leukocytes of hypersensitive individuals. II Reduced sensitivity of leukocytes after injection therapy. J. Allergy. 39:44, 1967.
18. Kin, T.P., P.S. Norman, and L.M. Lichtenstein. Isolation and characterization of allergens from ragweed pollen. IV, Biochemistry 6:1992, 1967.
19. Lichtenstein, L.M., P.S. Norman and W.L. Winkenwerder. A single year of immunotherapy for ragweed hay fever. Annals of Internal Medicine. 75:663, 1971.
20. Cooke, R.A. and A. Vander Veer, Jr., Human Sensitization. J. Immunology 1:201, 1916.
21. Vander Veer, A., R.A. Cooke and W.C. Spain. Diagnosis and treatment of seasonal hay fever. American J. Medical Science. 174:101, 1927.
22. Wodehouse, R.P. Patterns of allergic sensitization. Annals of Allergy. 6:358, 1948.
23. Wodehouse, R.P. Antigenic analysis of gel diffusion. I. Ragweed pollen. International Archives of Allergy. 5:425, 1954.
24. Prince, H.E. and P.G. Secrest. Immunologic relationship of giant, wester, common ragweed and marsh elder (Iva ciliate). J. Allergy 10:537, 1939.
25. Bernstein, I.L., M. Perera, J. Gallagher, J.G. Michael and S.G.O. Johansson. Invitro cross allergenicity of major aeroallergenic pollens by the radioallergosorbent technique. J. Allergy and Clinical Immunology. 57:141, 1976.
26. Leiferman, K., G.J. Gleich and R.T. Jones. The cross-reactivity of IgE antibodies with pollen allergens. II. Analysis of various species of ragweed and other fall weed pollens. J. Allergy and Clinical Immunolgoy. 58:140, 1976.
27. Simon, F.A. Allergenic relationship of the pollens of dwarf and giant ragweed to several of their botanic relatives. J. Experimental Medicine. 77:185, 1943.